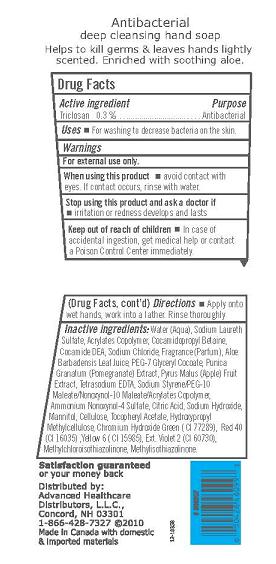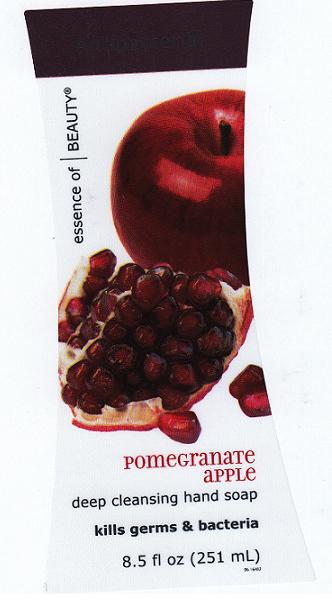 DRUG LABEL: Antibacterial
NDC: 59779-286 | Form: SOAP
Manufacturer: CVS Pharmacy 
Category: otc | Type: HUMAN OTC DRUG LABEL
Date: 20100824

ACTIVE INGREDIENTS: TRICLOSAN 0.3000 mL/100.0000 mL

Drug Facts Box - Back Panel

Active Ingredient

Triclosan 0.3%

Purpose

Antibacterial

Warnings

For external use only.

When using this product

- Avoid contact with eyes. If contact occurs, rinse with water.

Stop using this product and ask doctor if

- Irritation or redness develops and lasts.

Keep out of reach of children

In case of accidental ingestion, get medical help or contact a Poison Control Center immediately.

Uses

For washing to decrease bacteria on the skin.

Directions

Apply onto wet hands, work into a lather. Rinse thoroughly.

Inactive Ingredients

Water (Aqua), Sodium Laureth Sulfate, Acrylates Copolymer, Cocamidopropyl Betaine, Cocamide DEA, Sodium Chloride, Fragrance (Parfum), Aloe Barbadensis Leaf Juice, PEG-7 Glyceryl Cocoate, Punica Granatum (Pomegranate) Extract, Pyrus Malus (Apple) Fruit Extract, Tetrasodium EDTA, Sodium Styrene/PEG-10 Maleate/Nonoxynol-10 Maleate/ Acrylates Copolymer, Ammonium Nonoxynol-4 Sulfate, Citric Acid, Sodium Hydroxide, Mannitol, Cellulose, Tocopheryl Acetate, Hydroxypropyl Methylcellulose, Chromium Hydroxide Green (CI 77289), Red 40 (CI 16035), Ext. Violet 2 (CI 60730), Yellow 6 (CI 15985), Methylchloroisothiazolinone, Methylisothiazolinone.

PACKAGE FRONT AND BACK LABELS

- 8.5 OZ Front Panel Label: eobf.jpg
- 8.5 OZ Back Panel Label: eobb.jpg